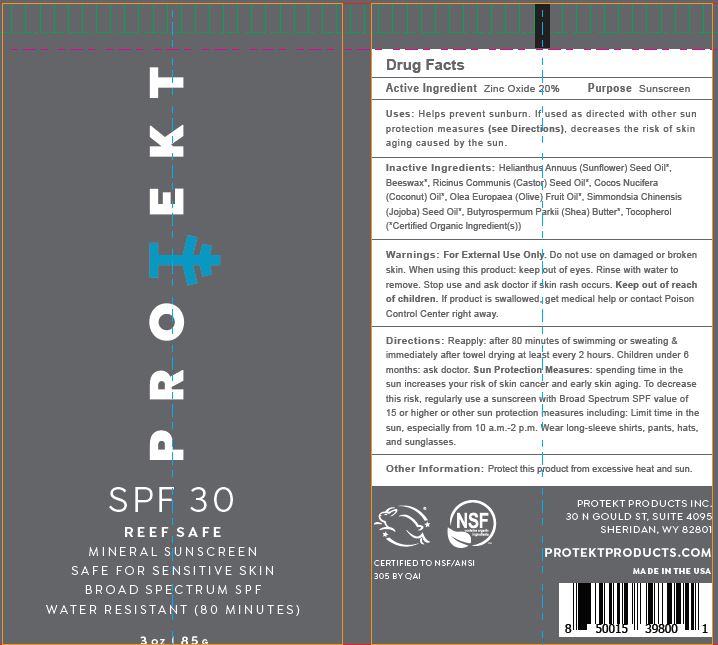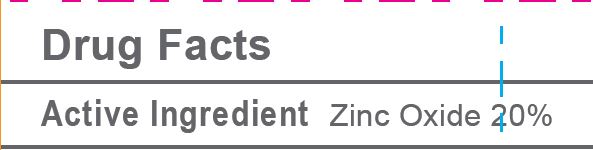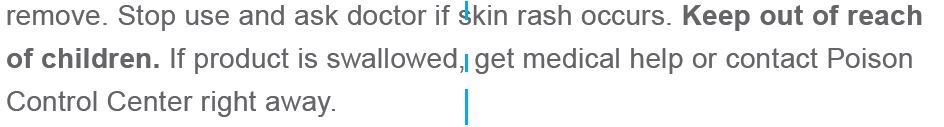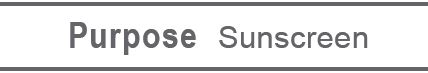 DRUG LABEL: LIP BALM
NDC: 62932-239 | Form: OINTMENT
Manufacturer: Private Label Select Ltd CO
Category: otc | Type: HUMAN OTC DRUG LABEL
Date: 20201230

ACTIVE INGREDIENTS: ZINC OXIDE 20 g/100 g
INACTIVE INGREDIENTS: .DELTA.-TOCOPHEROL; .BETA.-TOCOPHEROL; CASTOR OIL; OLIVE OIL; JOJOBA OIL; SUNFLOWER OIL; .ALPHA.-TOCOPHEROL, D-; .GAMMA.-TOCOPHEROL; WHITE WAX; SHEA BUTTER; COCONUT OIL

Protekt SPF 30 Mineral Sunscreen